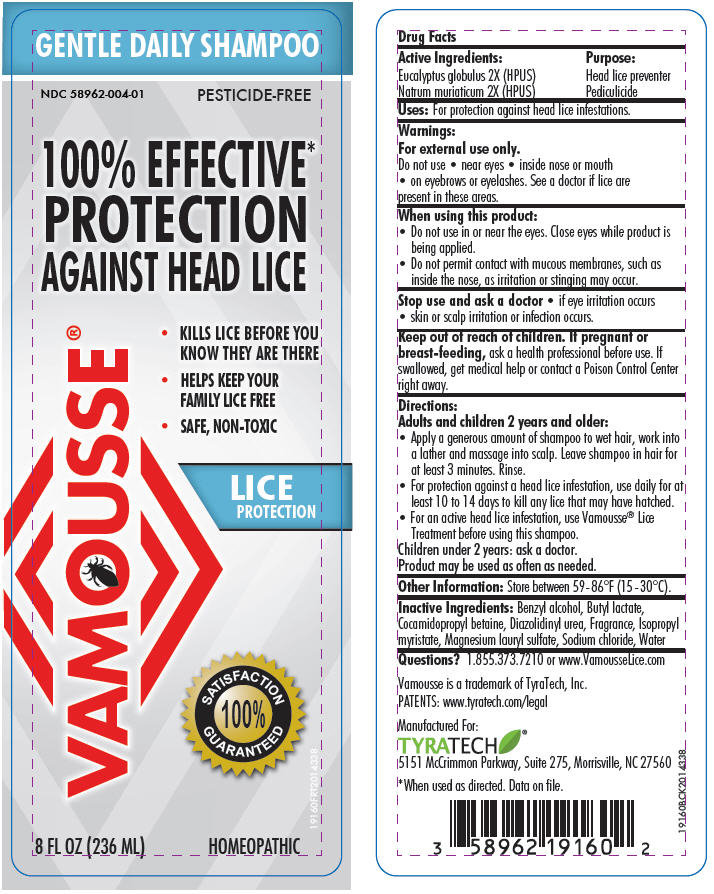 DRUG LABEL: Vamousse Lice Protection
NDC: 58962-004 | Form: SHAMPOO
Manufacturer: TyraTech, Inc.
Category: homeopathic | Type: HUMAN OTC DRUG LABEL
Date: 20150430

ACTIVE INGREDIENTS: EUCALYPTUS GLOBULUS LEAF 2 [hp_X]/1 mL; SODIUM CHLORIDE 2 [hp_X]/1 mL
INACTIVE INGREDIENTS: BENZYL ALCOHOL; BUTYL LACTATE; COCAMIDOPROPYL BETAINE; DIAZOLIDINYL UREA; GERANIOL; ISOPROPYL MYRISTATE; MAGNESIUM LAURYL SULFATE; WATER

Vamousse® Lice Protection Shampoo

Drug Facts

ACTIVE INGREDIENT

Active Ingredients: | Purpose:
Eucalyptus globulus 2X (HPUS) | Head lice preventer
Natrum muriaticum 2X (HPUS) | Pediculicide

Uses

For protection against head lice infestations.

Warnings

For external use only.

Do not use

- near eyes
- inside nose or mouth
- on eyebrows or eyelashes. See a doctor if lice are present in these areas.

When using this product:

- Do not use in or near the eyes. Close eyes while product is being applied.
- Do not permit contact with mucous membranes, such as inside the nose, as irritation or stinging may occur.

Stop use and ask a doctor

- if eye irritation occurs
- skin or scalp irritation or infection occurs.

Keep out of reach of children. If pregnant or breast-feeding, ask a health professional before use. If swallowed, get medical help or contact a Poison Control Center right away.

Directions

Adults and children 2 years and older:

- Apply a generous amount of shampoo to wet hair, work into a lather and massage into scalp. Leave shampoo in hair for at least 3 minutes. Rinse.
- For protection against a head lice infestation, use daily for at least 10 to 14 days to kill any lice that may have hatched.
- For an active head lice infestation, use Vamousse® Lice Treatment before using this shampoo.

Children under 2 years: ask a doctor.

Product may be used as often as needed.

Other Information

Store between 59-86°F (15 -30°C).

Inactive Ingredients

Benzyl alcohol, Butyl lactate, Cocamidopropyl betaine, Diazolidinyl urea, Fragrance, Isopropyl myristate, Magnesium lauryl sulfate, Sodium chloride, Water

Questions?

1.855.373.7210 or www.VamousseLice.com

PRINCIPAL DISPLAY PANEL - 236 mL Bottle Label

GENTLE DAILY SHAMPOO

NDC 58962-004-01
PESTICIDE-FREE

100% EFFECTIVE*
PROTECTION
AGAINST HEAD LICE

VAMOUSSE®

- KILLS LICE BEFORE YOU
  KNOW THEY ARE THERE
- HELPS KEEP YOUR
  FAMILY LICE FREE
- SAFE, NON-TOXIC

LICE
PROTECTION

SATISFACTION
100%
GUARANTEED

8 FL OZ (236 ML)
HOMEOPATHIC

19160FRT2014338